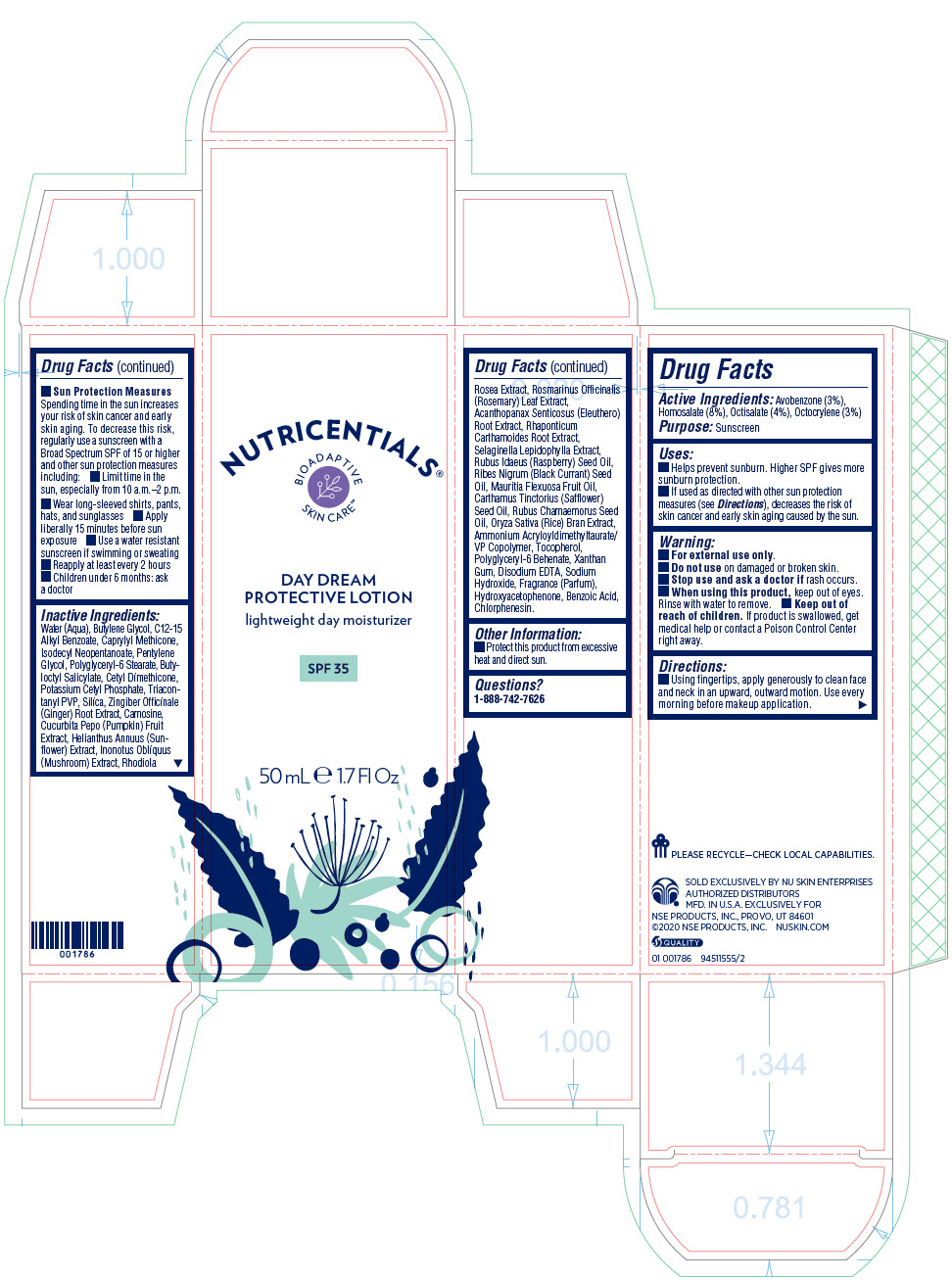 DRUG LABEL: Nutricentials Day Dream Protective
NDC: 62839-1555 | Form: LOTION
Manufacturer: NSE Products, Inc.
Category: otc | Type: HUMAN OTC DRUG LABEL
Date: 20220113

ACTIVE INGREDIENTS: Homosalate 80 mg/1 mL; Octisalate 40 mg/1 mL; Avobenzone 30 mg/1 mL; Octocrylene 30 mg/1 mL
INACTIVE INGREDIENTS: Water; Butylene Glycol; CAPRYLYL TRISILOXANE; ALKYL (C12-15) BENZOATE; Isodecyl Neopentanoate; Pentylene Glycol; Polyglyceryl-6 Stearate; Potassium Cetyl Phosphate; Butyloctyl Salicylate; TRICONTANYL POVIDONE; SILICON DIOXIDE; Ammonium Acryloyldimethyltaurate/VP Copolymer; POLYGLYCERYL-6 BEHENATE; HYDROXYACETOPHENONE; Chlorphenesin; Ginger; EDETATE DISODIUM ANHYDROUS; Carnosine; RICE BRAN; Benzoic Acid; RIBES NIGRUM SEED OIL; Mauritia Flexuosa Fruit Oil; Xanthan Gum; RASPBERRY SEED OIL; Rubus Chamaemorus Seed Oil; HELIANTHUS ANNUUS FLOWERING TOP; SEDUM ROSEUM ROOT; INONOTUS OBLIQUUS FRUITING BODY; ELEUTHERO; Rhaponticum Carthamoides Root; Tocopherol; Rosemary; SAFFLOWER OIL; PUMPKIN; Sodium Hydroxide

Nutricentials® Day Dream Protective Lotion

Drug Facts

Active Ingredients

Avobenzone (3%), Homosalate (8%), Octisalate (4%), Octocrylene (3%)

Purpose

Sunscreen

Uses

- Helps prevent sunburn. Higher SPF gives more sunburn protection.
- If used as directed with other sun protection measures (see Directions), decreases the risk of skin cancer and early skin aging caused by the sun.

Warning

- For external use only.

- Do not use on damaged or broken skin.

- Stop use and ask a doctor if rash occurs.

- When using this product, keep out of eyes. Rinse with water to remove.

- Keep out of reach of children. If product is swallowed, get medical help or contact a Poison Control Center right away.

Directions

- Using fingertips, apply generously to clean face and neck in an upward, outward motion. Use every morning before makeup application.
- Sun Protection Measures Spending time in the sun increases your risk of skin cancer and early skin aging. To decrease this risk, regularly use a sunscreen with a Broad Spectrum SPF of 15 or higher and other sun protection measures including:
  - Limit time in the sun, especially from 10 a.m.–2 p.m.
  - Wear long-sleeved shirts, pants, hats, and sunglasses
- Apply liberally 15 minutes before sun exposure
- Use a water resistant sunscreen if swimming or sweating
- Reapply at least every 2 hours
- Children under 6 months: ask a doctor

Inactive Ingredients

Water (Aqua), Butylene Glycol, C12-15 Alkyl Benzoate, Caprylyl Methicone, Isodecyl Neopentanoate, Pentylene Glycol, Polyglyceryl-6 Stearate, Butyloctyl Salicylate, Cetyl Dimethicone, Potassium Cetyl Phosphate, Triacontanyl PVP, Silica, Zingiber Officinale (Ginger) Root Extract, Carnosine, Cucurbita Pepo (Pumpkin) Fruit Extract, Helianthus Annuus (Sunflower) Extract, Inonotus Obliquus (Mushroom) Extract, Rhodiola Rosea Extract, Rosmarinus Officinalis (Rosemary) Leaf Extract, Acanthopanax Senticosus (Eleuthero) Root Extract, Rhaponticum Carthamoides Root Extract, Selaginella Lepidophylla Extract, Rubus Idaeus (Raspberry) Seed Oil, Ribes Nigrum (Black Currant) Seed Oil, Mauritia Flexuosa Fruit Oil, Carthamus Tinctorius (Safflower) Seed Oil, Rubus Chamaemorus Seed Oil, Oryza Sativa (Rice) Bran Extract, Ammonium Acryloyldimethyltaurate/ VP Copolymer, Tocopherol, Polyglyceryl-6 Behenate, Xanthan Gum, Disodium EDTA, Sodium Hydroxide, Fragrance (Parfum), Hydroxyacetophenone, Benzoic Acid, Chlorphenesin.

Other Information

- Protect this product from excessive heat and direct sun.

Questions?

1-888-742-7626

PRINCIPAL DISPLAY PANEL - 50 mL Tube Carton

NUTRICENTIALS®

BIOADAPTIVE
SKIN CARE™

DAY DREAM
PROTECTIVE LOTION

lightweight day moisturizer

SPF 35

50 mL e 1.7 Fl Oz